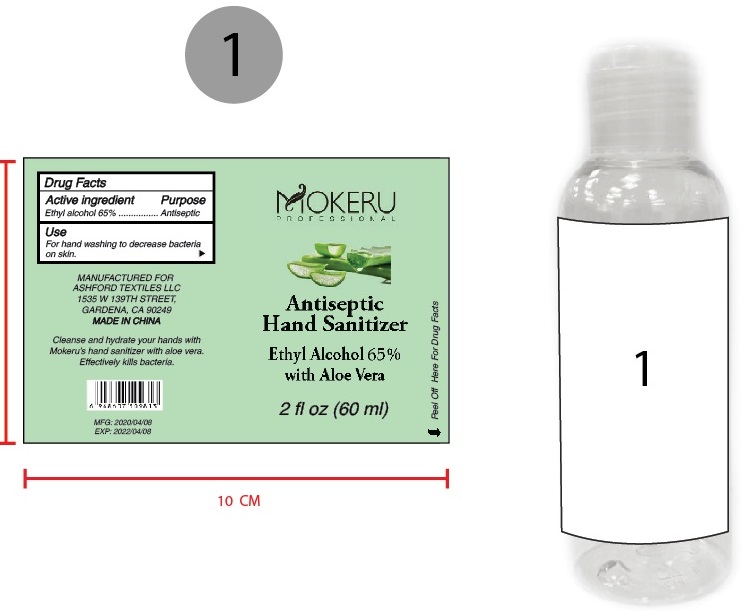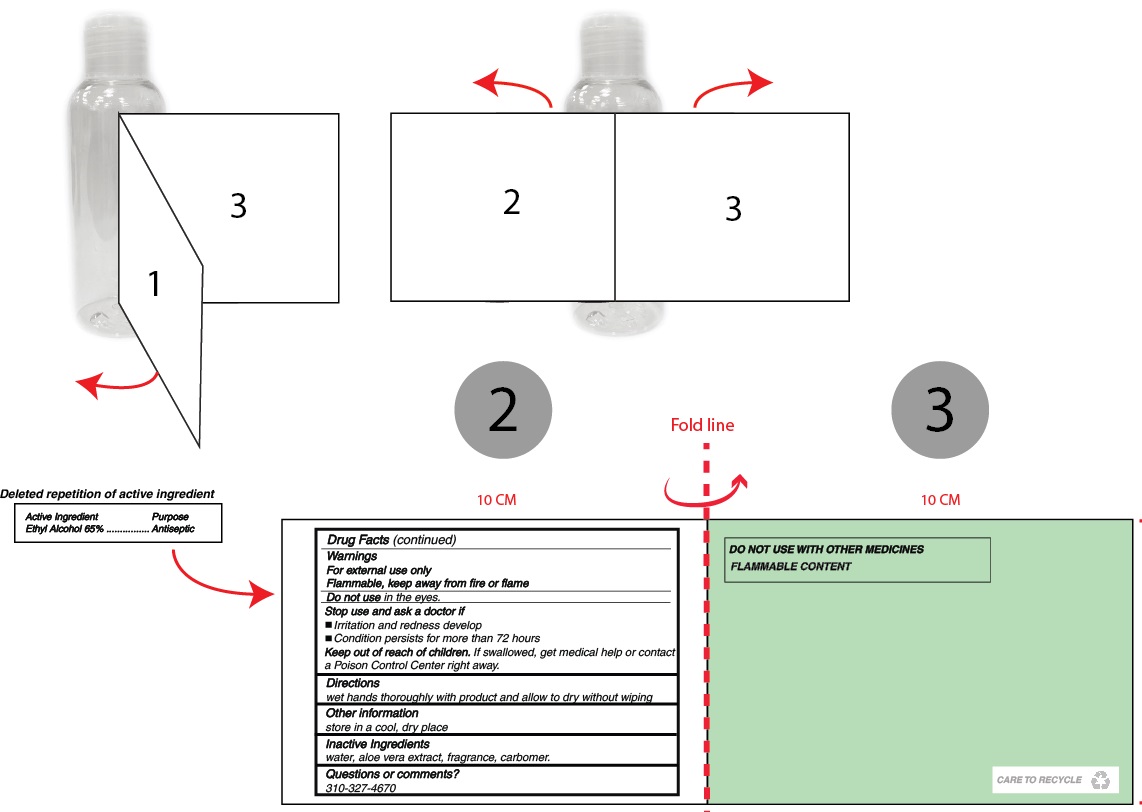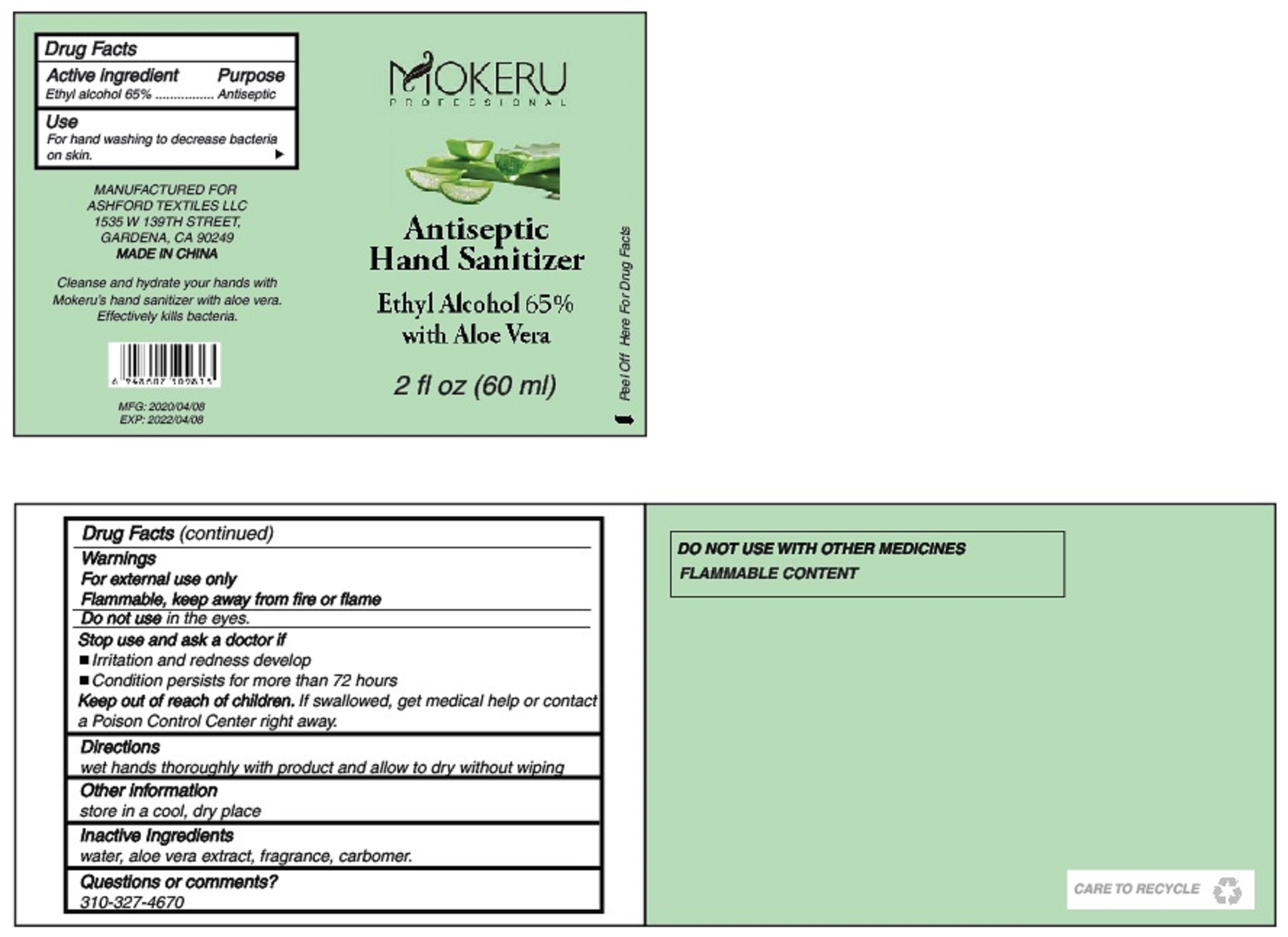 DRUG LABEL: Mokeru Antiseptic Hand Sanitizer
NDC: 78156-001 | Form: GEL
Manufacturer: Ashford Textiles LLC
Category: otc | Type: HUMAN OTC DRUG LABEL
Date: 20200617

ACTIVE INGREDIENTS: ALCOHOL 0.65 mL/1 mL
INACTIVE INGREDIENTS: WATER; ALOE VERA LEAF; CARBOMER HOMOPOLYMER, UNSPECIFIED TYPE

Mokeru Antiseptic Hand Sanitizer

Active ingredient

Ethyl alcohol 65%

Purpose

Antiseptic

Use

For hand washing to decrease bacteria on skin.

Warnings

For external use only

Flammable, keep away from fire or flame

Do not use

in the eyes.

Stop use and ask a doctor if

- Irritation and redness develop
- Condition persists for more than 72 hours

Keep out of reach of children.

If swallowed, get medical help or contact a Poison Control Center right away.

Directions

wet hands thoroughly with product and allow to dry without wiping

Other information

store in a cool, dry place

Inactive Ingredients

water, aloe vera extract, fragrance, carbomer.

Questions or comments?

310-327-4670